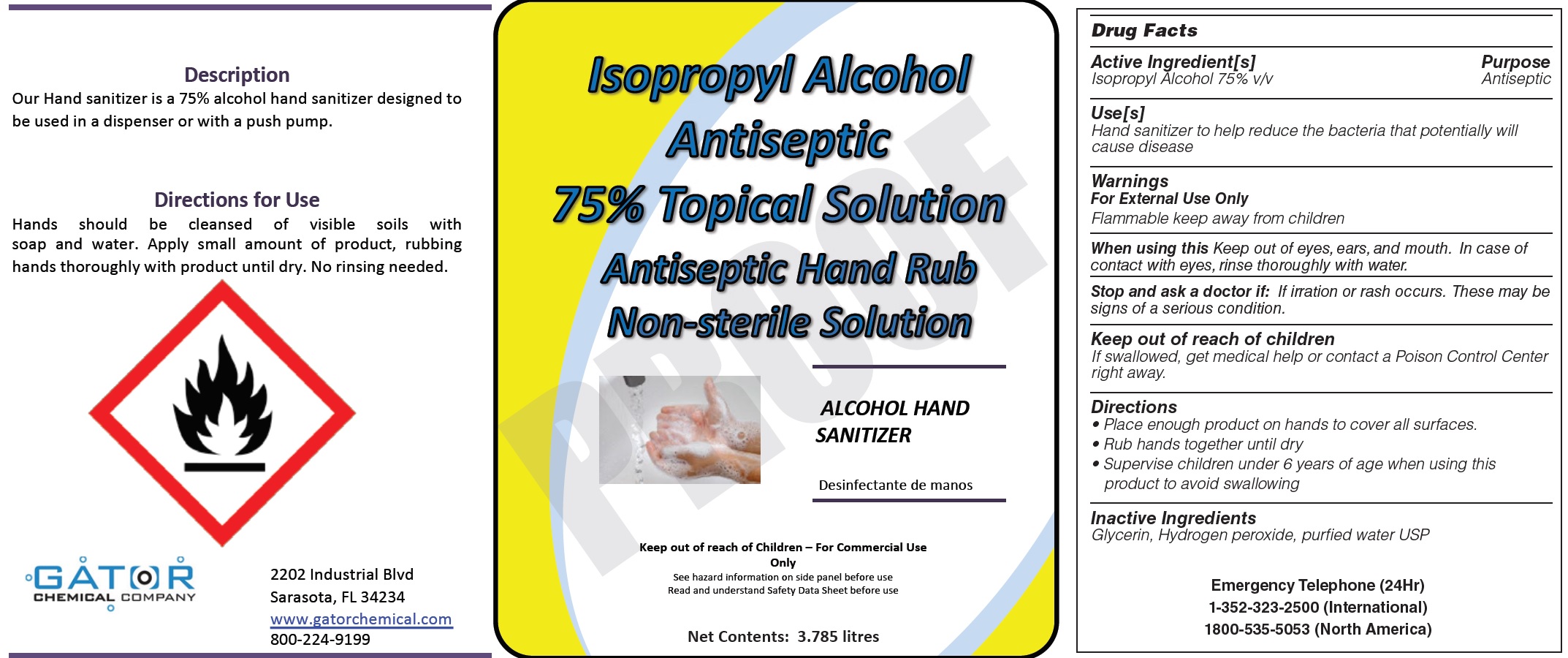 DRUG LABEL: Isopropyl Alcohol Antiseptic 75
NDC: 77188-001 | Form: LIQUID
Manufacturer: Resource One Inc
Category: otc | Type: HUMAN OTC DRUG LABEL
Date: 20200512

ACTIVE INGREDIENTS: ISOPROPYL ALCOHOL 0.75 mL/1 mL
INACTIVE INGREDIENTS: GLYCERIN; HYDROGEN PEROXIDE; WATER

Isopropyl Alcohol Antiseptic 75% Topical Solution

Active Ingredient[s]

Isopropyl Alcohol 75% v/v

Purpose:

Antiseptic

Use(s):

Hand sanitizer to help reduce the bacteria that potentially will cause disease

Warnings:

For External Use Only
Flammable keep away from children

When using this

Keep out of eyes, ears, and mouth. In case of contact with eyes, rinse thoroughly with water.

Stop and ask a doctor if:

If irration or rash occurs. These may be signs of a serious condition.

Keep out of reach of children:

If swallowed, get medical help or contact a Poison Control Center right away.

Directions:

- Place enough product on hands to cover all surfaces.
- Rub hands together until dry.
- Supervise children under 6 years of age when using this product to avoid swallowing

Inactive Ingredients:

Glycerin, Hydrogen peroxide, purified water USP